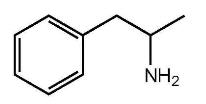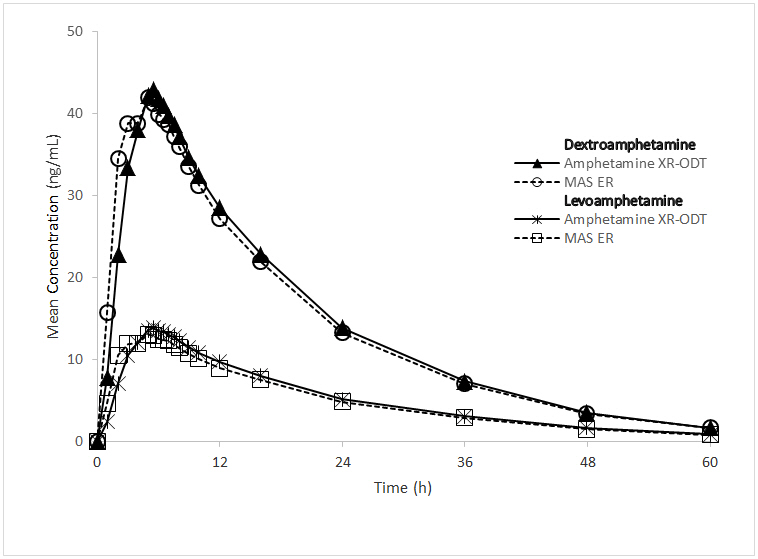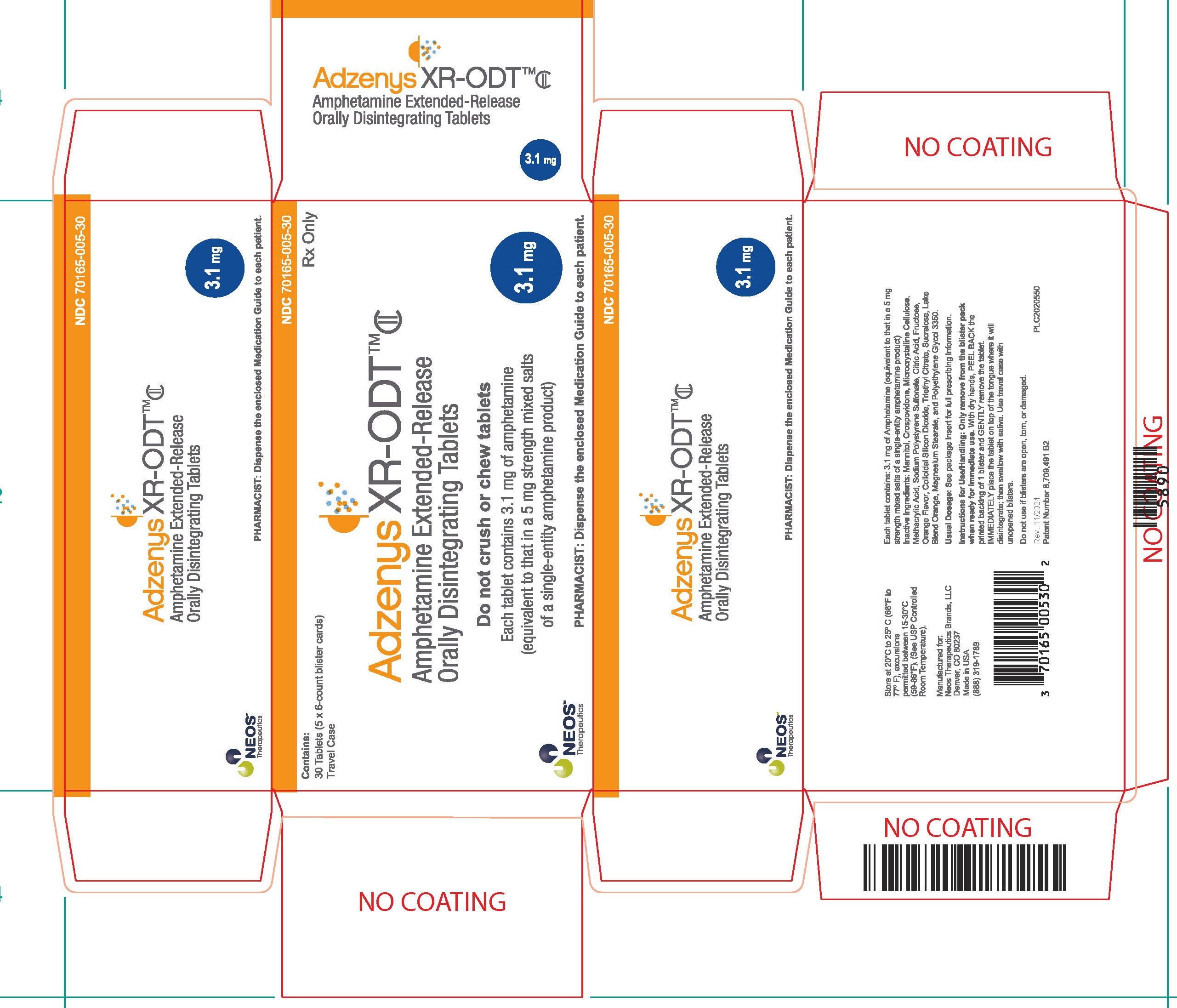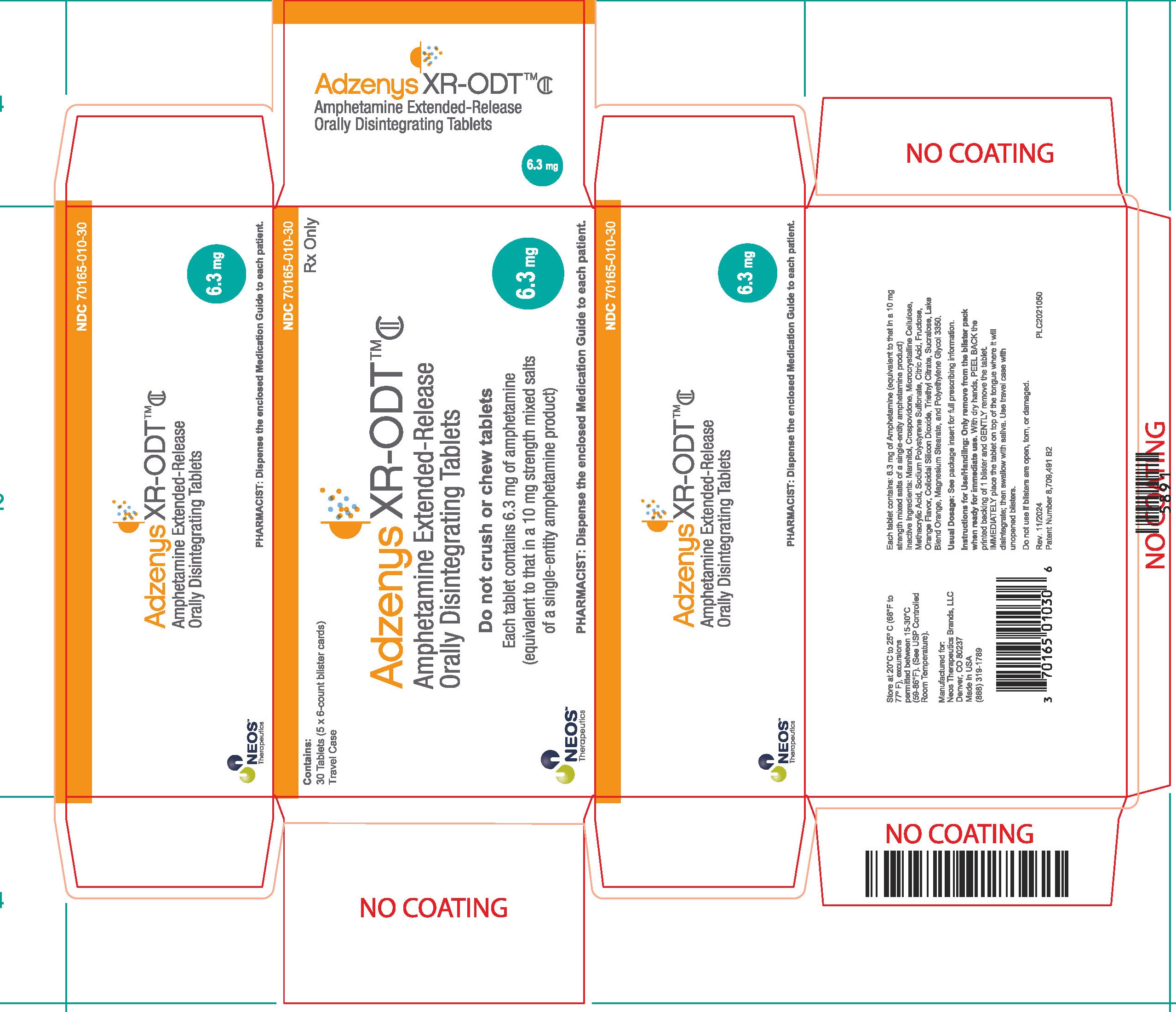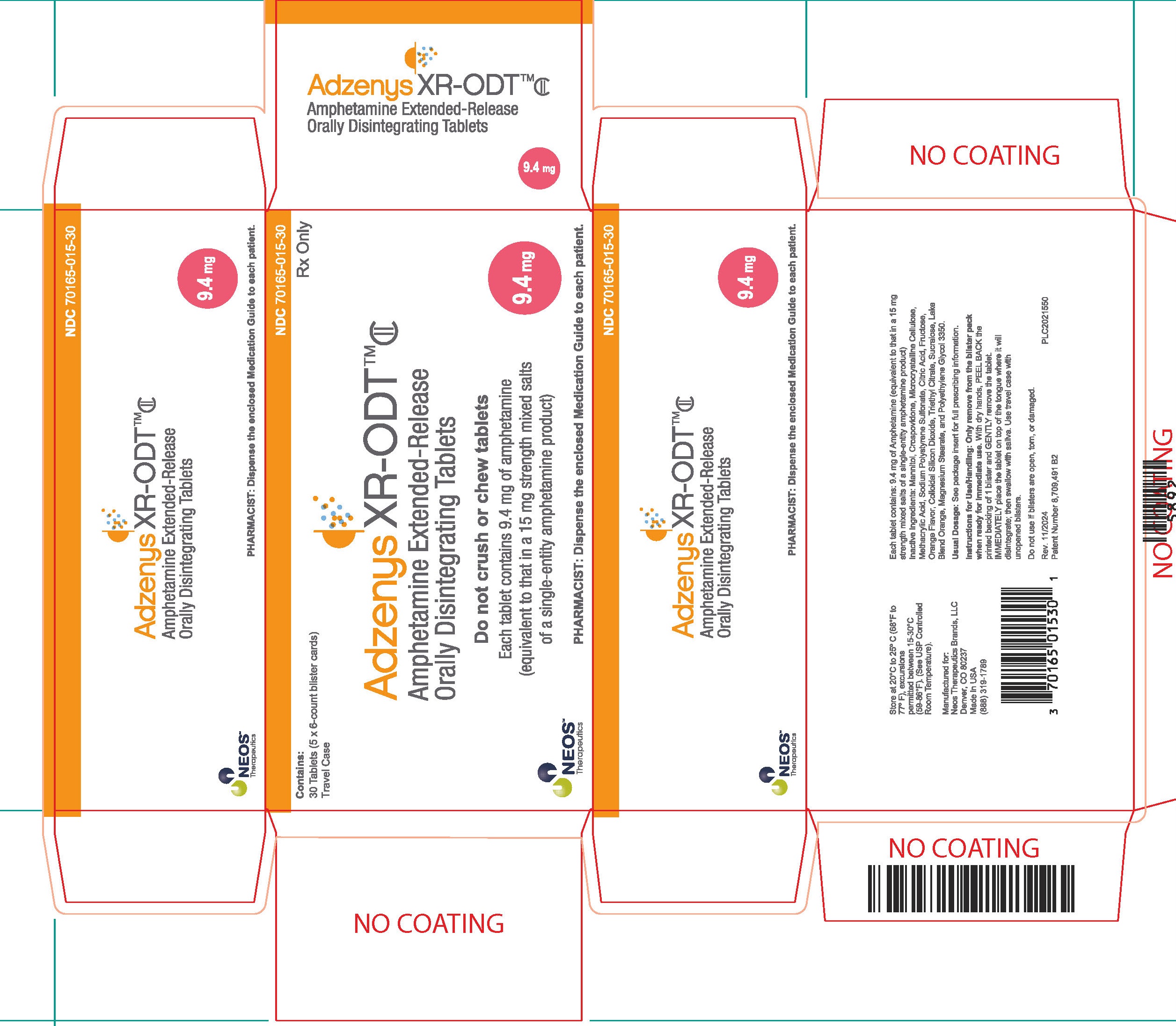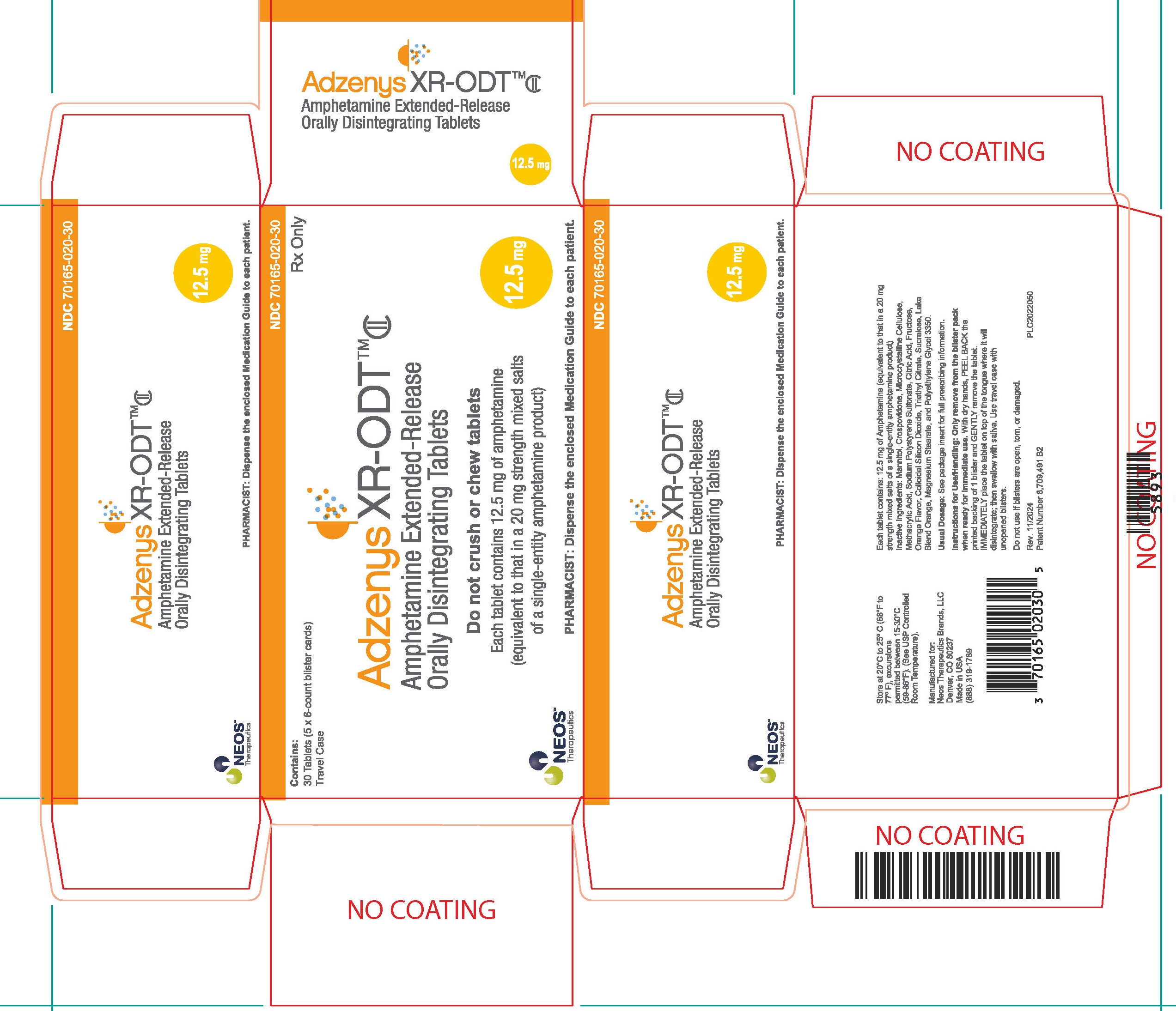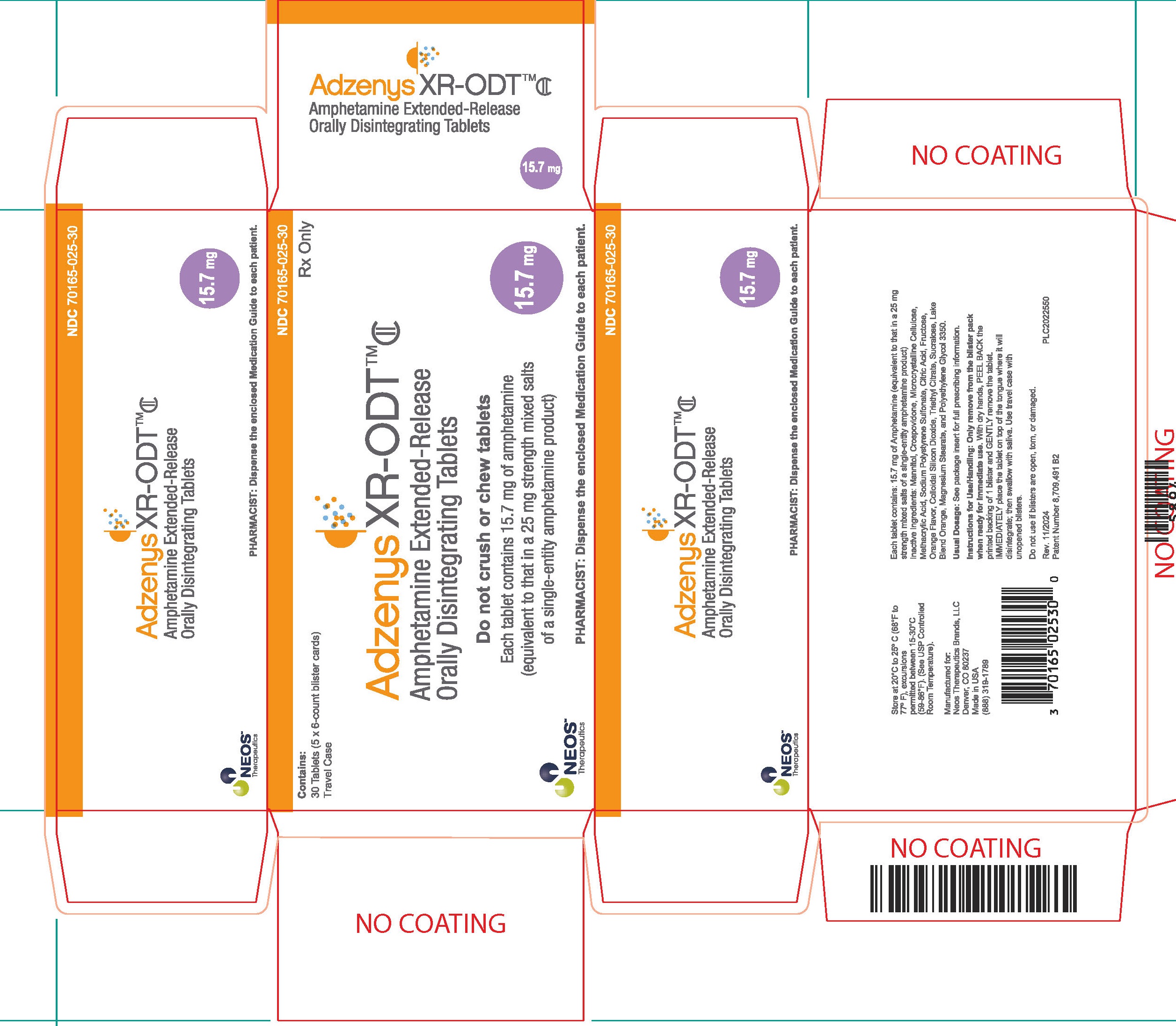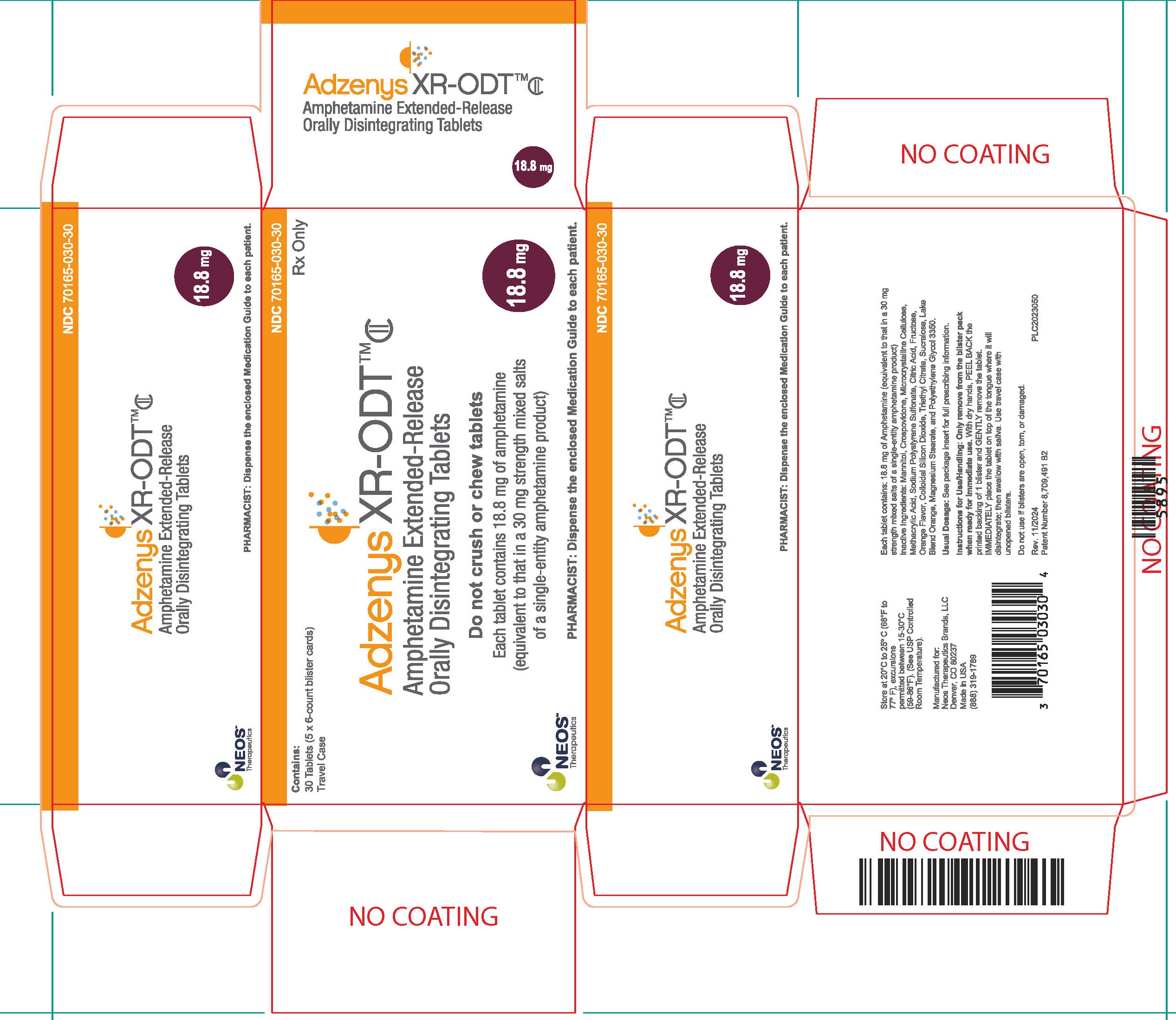 DRUG LABEL: Adzenys XR-ODT
NDC: 70165-030 | Form: TABLET, ORALLY DISINTEGRATING
Manufacturer: Neos Therapeutics Brands, LLC
Category: prescription | Type: HUMAN PRESCRIPTION DRUG LABEL
Date: 20250924
DEA Schedule: CII

ACTIVE INGREDIENTS: AMPHETAMINE 18.8 mg/1 1
INACTIVE INGREDIENTS: CROSPOVIDONE (15 MPA.S AT 5%); MICROCRYSTALLINE CELLULOSE; METHACRYLIC ACID; SODIUM POLYSTYRENE SULFONATE; CITRIC ACID MONOHYDRATE; FRUCTOSE; SILICON DIOXIDE; TRIETHYL CITRATE; SUCRALOSE; MAGNESIUM STEARATE; POLYETHYLENE GLYCOL, UNSPECIFIED; MANNITOL

HIGHLIGHTS OF PRESCRIBING INFORMATION

These highlights do not include all the information needed to use ADZENYS XR-ODT™ safely and effectively. See full prescribing information for ADZENYS XR-ODT.
ADZENYS XR-ODT (amphetamine) extended-release orally disintegrating tablets, CII
Initial U.S. Approval: 1960

1. INDICATIONS AND USAGE

ADZENYS XR-ODT is a central nervous system (CNS) stimulant indicated for the treatment of Attention Deficit Hyperactivity Disorder (ADHD) in patients 6 years and older. (1)

Limitations of Use

The use of ADZENYS XR-ODT is not recommended in pediatric patients younger than 6 years of age because they had higher plasma exposure and a higher incidence of adverse reactions (e.g., weight loss) than patients 6 years and older at the same dosage. (5.5, 8.4)

WARNING: ABUSE, MISUSE AND ADDICTION

See full prescribing information for complete boxed warning.

ADZENYS XR-ODT has a high potential for abuse and misuse, which can lead to the development of a substance use disorder, including addiction. Misuse and abuse of CNS stimulants, including ADZENYS XR-ODT, can result in overdose and death (5.1, 9.2, 10):

- Before prescribing ADZENYS XR-ODT, assess each patient's risk for abuse, misuse, and addiction.
- Educate patients and their families about these risks, proper storage of the drug, and proper disposal of any unused drug.
- Throughout treatment, reassess each patient's risk and frequently monitor for signs and symptoms of abuse, misuse, and addiction.

2. DOSAGE AND ADMINISTRATION

- May be taken with or without food. Allow tablet to disintegrate in saliva then swallow. (2.2)
- Pediatric patients (ages 6 to 17 years): Starting dose is 6.3 mg once daily in the morning. Maximum dose is 18.8 mg once daily for patients 6 to 12 years, and 12.5 mg once daily for patients 13 to 17 years. (2.3)
- Adults: 12.5 mg once daily in the morning. (2.4)
- To avoid substitution errors and overdosage, do not substitute for other amphetamine products on a milligram-per-milligram basis because of different amphetamine base compositions and differing pharmacokinetic profiles. (2.5, 5.7)

4. CONTRAINDICATIONS

- Known hypersensitivity to amphetamine products or other ingredients in ADZENYS XR-ODT. (4)
- Use of monoamine oxidase inhibitor (MAOI) or within 14 days of the last MAOI dose. (4)

3. DOSAGE FORMS AND STRENGTHS

Extended-release orally disintegrating tablets: 3.1 mg, 6.3 mg, 9.4 mg, 12.5 mg, 15.7 mg, 18.8 mg (3)

5. WARNINGS AND PRECAUTIONS

- Risks to Patients with Serious Cardiac Disease: Avoid use in patients with known structural cardiac abnormalities, cardiomyopathy, serious heart arrhythmia, coronary artery disease, or other serious cardiac disease. (5.2)
- Increased Blood Pressure and Heart Rate: Monitor blood pressure and pulse. (5.3)
- Psychiatric Adverse Reactions: Prior to initiating ADZENYS XR-ODT, screen patients for risk factors for developing a manic episode. If new psychotic or manic symptoms occur, consider discontinuing ADZENYS XR-ODT. (5.4)
- Long-Term Suppression of Growth in Pediactric Patients: Closely monitor growth (height and weight) in pediatric patients. Pediatric patients not growing or gaining height or weight as expected may need to have their treatment interrupted. (5.5)
- Peripheral Vasculopathy, including Raynaud's phenomenon: Careful observation for digital changes is necessary during ADZENYS XR-ODT treatment. Further clinical evaluation (e.g. rheumatology referral) may be appropriate for patients who develop signs or symptoms of peripheral vasculopathy. (5.6)
- Serotonin Syndrome: Increased risk when co-administered with serotonergic agents (e.g., SSRIs, SNRIs, triptans), but also during overdosage situations. If it occurs, discontinue ADZENYS XR-ODT and initiate supportive treatment. (5.7, 17)
- Motor and Verbal Tics, and Worsening of Tourette’s Syndrome: Before initiating ADZENYS XR-ODT, assess the family history and clinically evaluate patients for tics or Tourette’s syndrome. Regularly monitor patients for the emergence or worsening of tics or Tourette’s syndrome. Discontinue treatment if clinically appropriate. (5.8)

6. ADVERSE REACTIONS

- Pediatric patients ages 6 to 12 years: Most common adverse reactions (≥5% and with a higher incidence than on placebo) were loss of appetite, insomnia, abdominal pain, emotional lability, vomiting, nervousness, nausea, and fever. (6.1)
- Pediatric patients ages 13 to 17 years: Most common adverse reactions (≥5% and with a higher incidence than on placebo) were loss of appetite, insomnia, abdominal pain, weight loss, and nervousness. (6.1)
- Adults: Most common adverse reactions ≥5% and with a higher incidence than on placebo were dry mouth, loss of appetite, insomnia, headache, weight loss, nausea, anxiety, agitation, dizziness, tachycardia, diarrhea, asthenia, and urinary tract infections. (6.1)

To report SUSPECTED ADVERSE REACTIONS, contact Neos Therapeutics, Inc. at 1-888-319-1789 or http://www.adzenysxrodt.com or FDA at 1-800-FDA-1088 or www.fda.gov/medwatch.

7. DRUG INTERACTIONS

Acidifying and Alkalinizing Agents: Agents that alter urinary pH can alter blood levels of amphetamine. Acidifying agents can decrease amphetamine blood levels, while alkalinizing agents can increase amphetamine blood levels. Adjust ADZENYS XR-ODT dosage accordingly. (7.1)

8. USE IN SPECIFIC POPULATIONS

- Pregnancy: May cause fetal harm. (8.1)
- Lactation: Breastfeeding not recommended. (8.2)

RECENT MAJOR CHANGES

Indications and Usage (1) 09/2025

Warnings and Precautions (5.5) 09/2025

FULL PRESCRIBING INFORMATION

1. INDICATIONS AND USAGE

ADZENYS XR-ODT is a central nervous system (CNS) stimulant indicated for the treatment of Attention Deficit Hyperactivity Disorder (ADHD) in patients 6 years and older [see Clinical Studies (14)].

Limitations of Use

The use of ADZENYS XR-ODT is not recommended in pediatric patients younger than 6 years of age because they had higher plasma exposure and a higher incidence of adverse reactions (e.g. weight loss) than patients 6 years and older at the same dosage [see Warnings and Precautions (5.5). Use in Specific Populations (8.4)].

WARNING: ABUSE, MISUSE AND ADDICTION

ADZENYS XR-ODT has a high potential for abuse and misuse, which can lead to the development of a substance use disorder, including addiction. Misuse and abuse of CNS stimulants, including ADZENYS XR-ODT, can result in overdose and death [see Overdosage (10)], and this risk is increased with higher doses or unapproved methods of administration, such as snorting or injection.
Before prescribing ADZENYS XR-ODT, assess each patient’s risk for abuse, misuse, and addiction. Educate patients and their families about these risks, proper storage of the drug, and proper disposal of any unused drug. Throughout ADZENYS XR-ODT treatment, reassess each patient’s risk of abuse, misuse, and addiction and frequently monitor for signs and symptoms of abuse, misuse, and addiction [see Warnings and Precautions (5.1), Drug Abuse and Dependence (9.2)].

2. DOSAGE AND ADMINISTRATION

2.1 Pre-treatment Screening

Prior to treating patients with ADZENYS XR-ODT, assess:

- for the presence of cardiac disease (i.e., perform a careful history, family history of sudden death or ventricular arrhythmia, and physical exam) [see Warnings and Precautions (5.2)].
- the family history and clinically evaluate patients for motor or verbal tics or Tourette’s syndrome before initiating ADZENYS XR-ODT [see Warnings and Precautions (5.9)].

2.3 Dosage Recommendations in Pediatric Patients

The recommended starting dosage is 6.3 mg once daily in the morning. Increase in increments of 3.1 mg or 6.3 mg at weekly intervals. The maximum recommended dose is 18.8 mg daily for patients 6 to 12 years, and 12.5 mg daily for patients 13 to 17 years [see Use in Specific Populations (8.3), Clinical Studies (14)].

2.4 Dosage Recommendations in Adults

The recommended dose is ADZENYS XR-ODT 12.5 mg daily.

2.2 General Administration Information

ADZENYS XR-ODT may be taken orally with or without food. Individualize the dosage according to the therapeutic needs and response of the patient.

ADZENYS XR-ODT should be taken as follows:

- The tablet should remain in the blister pack until the patient is ready to take it.
- The patient or caregiver should use dry hands to open the blister.
- Tear along the perforation, bend the blister where indicated and peel back the blister's labeled backing to take out the tablet. The tablet should not be pushed through the foil.

As soon as the blister is opened, the tablet should be removed and placed on the patient's tongue.

- The whole tablet should be placed on the tongue and allowed to disintegrate without chewing or crushing.
- The tablet will disintegrate in saliva so that it can be swallowed.

2.5 Switching from Other Amphetamine Products

Patients taking ADDERALL XR may be switched to ADZENYS XR-ODT at the equivalent dose taken once daily [see Clinical Pharmacology (12.3)]. Refer to Table 1 for equivalent doses of ADZENYS XR-ODT and ADDERALL XR. ADDERALL XR (dextroamphetamine sulfate, dextroamphetamine saccharate, amphetamine aspartate monohydrate, and amphetamine sulfate extended-release capsules) is also referred to as mixed salts of a single-entity amphetamine product extended-release capsules (MAS ER).

Table 1: Equivalent Doses of ADZENYS XR-ODT and ADDERALL XR (Mixed Salts of a Single-Entity Amphetamine Product) Extended-Release Capsules
ADZENYS XR-ODT Amphetamine extended-release orally disintegrating tablets | 3.1 mg | 6.3 mg | 9.4 mg | 12.5 mg | 15.7 mg | 18.8 mg
ADDERALL XR Mixed salts of a single-entity amphetamine product extended-release capsules (MAS ER) | 5 mg | 10 mg | 15 mg | 20 mg | 25 mg | 30 mg

If switching from any other amphetamine products, discontinue that treatment, and titrate with ADZENYS XR-ODT using the titration schedule [ see Dosage and Administration (2.3), (2.4)].

Do not substitute for other amphetamine products on a milligram-per-milligram basis because of different amphetamine base compositions and differing pharmacokinetic profiles [see Warnings and Precautions (5.7)].

2.6 Dosage Modifications Due to Drug Interactions

Agents that alter urinary pH can impact urinary excretion and alter blood levels of amphetamine. Acidifying agents (e.g., ascorbic acid) decrease blood levels, while alkalinizing agents (e.g., sodium bicarbonate) increase blood levels. Adjust ADZENYS XR-ODT dosage accordingly [see Drug Interactions (7.1)].

4. CONTRAINDICATIONS

ADZENYS XR-ODT is contraindicated:

- In patients known to be hypersensitive to amphetamine, or other components of ADZENYS XR-ODT. Hypersensitivity reactions such as angioedema and anaphylactic reactions have been reported in patients treated with other amphetamine products [see Adverse Reactions (6.2)].
- Patients taking monoamine oxidase inhibitors (MAOIs), or within 14 days of stopping MAOIs (including MAOIs such a linezolid or intravenous methylene blue), because of an increased risk of hypertensive crisis [see Warnings and Precautions (5.7), Drug Interactions 7.1].

3. DOSAGE FORMS AND STRENGTHS

ADZENYS XR-ODT 3.1 mg Amphetamine extended release orally disintegrating tablet: round, orange to light orange mottled (debossed A1 on one side)

ADZENYS XR-ODT 6.3 mg Amphetamine extended release orally disintegrating tablet: round, orange to light orange mottled (debossed A2 on one side)

ADZENYS XR-ODT 9.4 mg Amphetamine extended release orally disintegrating tablet: round, orange to light orange mottled (debossed A3 on one side)

ADZENYS XR-ODT 12.5 mg Amphetamine extended release orally disintegrating tablet: round, orange to light orange mottled (debossed A4 on one side)

ADZENYS XR-ODT 15.7 mg Amphetamine extended release orally disintegrating tablet: round, orange to light orange mottled (debossed A5 on one side)

ADZENYS XR-ODT 18.8 mg Amphetamine extended release orally disintegrating tablet: round, orange to light orange mottled (debossed A6 on one side)

5. WARNINGS AND PRECAUTIONS

.

5.1 Abuse, Misuse, and Addiction

ADZENYS XR-ODT has a high potential for abuse and misuse. The use of ADZENYS XR-ODT exposes individuals to the risks of abuse and misuse, which can lead to the development of a substance use disorder, including addiction. ADZENYS XR-ODT can be diverted for nonmedical use into illicit channels or distribution [see Drug Abuse and Dependence (9.2)]. Misuse and abuse of CNS stimulants, including ADZENYS XR-ODT, can result in overdose and death [see Overdosage (10)], and this risk is increased with higher doses or unapproved methods of administration, such as snorting or injection.

Before prescribing ADZENYS XR-ODT, assess each patient’s risk for abuse, misuse, and addiction. Educate patients and their families about these risks and proper disposal of any unused drug. Advise patients to store ADZENYS XR-ODT in a safe place, preferably locked, and instruct patients to not give ADZENYS XR-ODT to anyone else. Throughout ADZENYS XR-ODT treatment, reassess each patient’s risk of abuse, misuse, and addiction and frequently monitor for signs and symptoms of abuse, misuse, and addiction.

5.2 Risks to Patients with Serious Cardiac Disease

Sudden death has been reported in patients with structural cardiac abnormalities or other serious cardiac disease who were treated with CNS stimulants at the recommended ADHD dosage.

Avoid ADZENYS XR-ODT use in patients with known structural cardiac abnormalities, cardiomyopathy, serious cardiac arrhythmia, coronary artery disease, or other serious cardiac disease.

5.3 Increased Blood Pressure and Heart Rate

CNS stimulants cause an increase in blood pressure (mean increase about 2 to 4 mm Hg) and heart rate (mean increase about 3 to 6 bpm). Some patients may have larger increases.

Monitor all ADZENYS XR-ODT-treated patients for potential tachycardia and hypertension.

5.4 Psychiatric Adverse Reactions

Exacerbation Pre-existing Psychosis

CNS stimulants may exacerbate symptoms of behavior disturbance and thought disorder in patients with a pre-existing psychotic disorder.

Induction of a Manic Episode in Patients with Bipolar Disorder

CNS stimulants may induce a manic or mixed episode in patients. Prior to initiating ADZENYS XR-ODT treatment, screen patients for risk factors for developing a manic episode (e.g., comorbid or has a history of depressive symptoms or a family history of suicide, bipolar disorder, and depression).

New Psychotic or Manic Symptoms

CNS stimulants, at the recommended dosages, may cause psychotic or manic symptoms, e.g., hallucinations, delusional thinking, or mania in patients without prior history of psychotic illness or mania. In a pooled analysis of multiple short-term, placebo-controlled studies of CNS stimulants, psychotic or manic symptoms occurred in 0.1% of CNS stimulant-treated patients compared to 0% of placebo-treated patients. If such symptoms occur, conisder discontinuing ADZENYS XR-ODT.

5.5 Long-Term Suppression of Growth in Pediatric Patients

ADZENYS XR-ODT is not approved for use and is not recommended in pediatric patients below 6 years of age [see Use in Specific Population (8.4)].

CNS stimulants have been associated with weight loss and slowing of growth rate in pediatric patients. Closely monitor growth (weight and height) in ADZENYS XR-ODT-treated pediatric patients treated with CNS stimulants.

Pediatric patients not growing or gaining height or weight as expected may need to have their treatment interrupted.

5.6 Peripheral Vasculopathy, including Raynaud's Phenomenon

CNS stimulants, including ADZENYS XR-ODT, used to treat ADHD are associated with peripheral vasculopathy, including Raynaud's phenomenon. Signs and symptoms are usually intermittent and mild; however, sequelae have included digital ulceration and/or soft tissue breakdown. Effects of peripheral vasculopathy, including Raynaud's phenomenon, were observed in post-marketing reports and at the therapeutic dosage of CNS stimulants in all age groups throughout the course of treatment. Signs and symptoms generally improved after dosage reduction or discontinuation of the CNS stimulants.

Careful observation for digital changes is necessary during ADZENYS XR-ODT-treatment. Further clinical evaluation (e.g., rheumatology referral) may be appropriate for ADZENYS XRODT-treated patients who develop signs or symptoms of peripheral vasculopathy.

5.7 Serotonin Syndrome

Serotonin syndrome, a potentially life-threatening reaction, may occur when amphetamines are used in combination with other drugs that affect the serotonergic neurotransmitter systems such as monoamine oxidase inhibitors (MAOIs), selective serotonin reuptake inhibitors (SSRIs), serotonin norepinephrine reuptake inhibitors (SNRIs), triptans, tricyclic antidepressants, fentanyl, lithium, tramadol, tryptophan, buspirone, and St. John's Wort [see Drug Interactions (7.1)]. The co-administration with cytochrome P450 2D6 (CYP2D6) inhibitors may also increase the risk with increased exposure to ADZENYS XR-ODT. In these situations, consider an alternative non-serotonergic drug or an alternative drug that does not inhibit CYP2D6 [see Drug Interactions (7.1)].

Serotonin syndrome symptoms may include mental status changes (e.g., agitation, hallucinations, delirium, and coma), autonomic instability (e.g., tachycardia, labile blood pressure, dizziness, diaphoresis, flushing, hyperthermia), neuromuscular symptoms (e.g., tremor, rigidity, myoclonus, hyperreflexia, incoordination), seizures, and/or gastrointestinal symptoms (e.g., nausea, vomiting, diarrhea).

Concomitant use of ADZENYS XR-ODT with MAOI drugs is contraindicated [see Contraindications (4)].

Discontinue treatment with ADZENYS XR-ODT and any concomitant serotonergic agents immediately if the above symptoms occur, and initiate supportive symptomatic treatment. If concomitant use of ADZENYS XR-ODT with other serotonergic drugs or CYP2D6 inhibitors is clinically warranted, initiate ADZENYS XR-ODT with lower doses, monitor patients for the emergence of serotonin syndrome during drug initiation or titration, and inform patients of the increased risk for serotonin syndrome.

5.8 Motor and Verbal Tics, and Worsening of Tourette’s Syndrome

CNS stimulants, including amphetamine, have been associated with the onset or exacerbation of motor and verbal tics. Worsening of Tourette’s syndrome has also been reported [see Adverse Reactions (6.2)].

Before initiating ADZENYS XR-ODT, assess the family history and clinically evaluate patients for tics or Tourette’s syndrome. Regularly monitor ADZENYS XR-ODT-treated patients for the emergence or worsening of tics or Tourette’s syndrome and discontinue treatment if clinically appropriate.

5.9 Potential for Overdose Due to Medication Errors

Medication errors, including substitution and dispensing errors, between ADZENYS XR-ODT and other amphetamine products could occur, leading to possible overdosage. To avoid substitution errors and overdosage, do not substitute for other amphetamine products on a milligram-per-milligram basis because of different amphetamine base compositions and differing pharmacokinetic profiles [see Dosage and Administration (2.5)].

6. ADVERSE REACTIONS

The following adverse reactions are discussed in greater detail in other sections of the labeling:

- Abuse, Misuse, and Addiction [see Boxed Warning, Warnings and Precautions (5.1), and Drug Abuse and Dependence (9.2, 9.3)]
- Hypersensitivity to amphetamine, or other components of ADZENYS XR-ODT [see Contraindications (4)]
- Hypertensive Crisis When Used Concomitantly with Monoamine Oxidase Inhibitors [see Contraindications (4) and Drug Interactions (7.1)]
- Risks to Patients with Serious Cardiac Disease [see Warnings and Precautions (5.2)]
- Increased Blood Pressure and Heart Rate [see Warnings and Precautions (5.3)]
- Psychiatric Adverse Reactions [see Warnings and Precautions (5.4)]
- Long-Term Suppression of Growth in Pediatric Patients [see Warnings and Precautions (5.5)]
- Peripheral Vasculopathy, including Raynaud's phenomenon [see Warnings and Precautions (5.6)]
- Serotonin Syndrome [ see Warnings and Precautions (5.7)]
- Motor and Verbal Tics, and Worsening of Tourette's Syndrome [ see Warnings and Precautions (5.8) ]

6.1 Clinical Trials Experience

Because clinical trials are conducted under widely varying conditions, adverse reaction rates observed in the clinical trials of a drug cannot be directly compared to rates in the clinical trials of another drug and may not reflect the rates observed in clinical practice.

The safety of ADZENYS XR-ODT has been established from adequate and well-controlled studies of single-entity amphetamine product extended-release (MAS ER) capsules [see Clinical Studies (14)]. The adverse reactions of MAS ER capsules in these adequate and well-controlled studies are described below.

The premarketing development program for MAS ER included exposures in a total of 1315 participants in clinical trials (635 pediatric patients, 350 adolescent patients, 248 adult patients, and 82 healthy adult subjects). Of these, 635 patients (ages 6 to 12 years) were evaluated in two controlled clinical studies, one open-label clinical study, and two single-dose clinical pharmacology studies (N= 40).

Adverse Reactions Leading to Discontinuation of Treatment

The most frequent adverse reactions leading to discontinuation of MAS ER in controlled and uncontrolled, multiple-dose clinical trials of pediatric patients ages 6 to 12 years (N=595) were anorexia (loss of appetite) (2.9%), insomnia (1.5%), weight loss (1.2%), emotional lability (1%), and depression (0.7%).

In a separate placebo-controlled 4-week study in pediatric patients ages 13 to 17 years with ADHD, five patients (2.1%) discontinued treatment due to adverse events among MAS ER-treated patients (N=233) compared to 0% who received placebo (N=54). The most frequent adverse event leading to discontinuation and considered to be drug-related (i.e., leading to discontinuation in at least 1% of MAS ER-treated patients and at a rate at least twice that of placebo) was insomnia (1.3%, n=3).

In one placebo-controlled 4-week study among adults with ADHD with doses 20 mg to 60 mg, 23 patients (12.0%) discontinued treatment due to adverse events among MAS ER-treated patients (N=191) compared to one patient (1.6%) who received placebo (N=64). The most frequent adverse events leading to discontinuation and considered to be drug-related (i.e., leading to discontinuation in at least 1% of MAS ER-treated patients and at a rate at least twice that of placebo) were insomnia (5.2%, n=10), anxiety (2.1%, n=4), nervousness (1.6%, n=3), dry mouth (1.6%, n=3), anorexia (1.6%, n=3), tachycardia (1.6%, n=3), headache (1.6%, n=3), and asthenia (1.0%, n=2).

Adverse Reactions Occurring in Clinical Trials

Adverse reactions reported in a 3-week clinical trial of pediatric patients 6 to 12 years of age and a 4-week clinical trial in pediatric patients 13 to 17 years of age and adults, respectively, treated with MAS ER or placebo are presented in the tables below.

Table 2: Adverse Reactions Reported by 2% or More of Pediatric Patients (6-12 years old) Receiving MAS ER with Higher Incidence than on Placebo in a 584-Patient Clinical Study
Body System | Adverse Reaction | MAS ER (n=374) | Placebo (n=210)
General | Abdominal Pain (stomachache) | 14% | 10%
 | Fever | 5% | 2%
 | Infection | 4% | 2%
 | Accidental Injury | 3% | 2%
 | Asthenia (fatigue) | 2% | 0%
Digestive System | Loss of Appetite | 22% | 2%
 | Vomiting | 7% | 4%
 | Nausea | 5% | 3%
 | Dyspepsia | 2% | 1%
Nervous System | Insomnia | 17% | 2%
 | Emotional Lability | 9% | 2%
 | Nervousness | 6% | 2%
 | Dizziness | 2% | 0%
Metabolic/Nutritional | Weight Loss | 4% | 0%

Table 3: Adverse Reactions Reported by 5% or More of Pediatric Patients (13-17 Years Old) Weighing ≤ 75kg Receiving MAS ER with Higher Incidence than Placebo in a 287 Patient Clinical Forced Weekly-Dose Titration Study [Included doses up to 40 mg]
Body System | Preferred Term | MAS ER (n=233) | Placebo (n=54)
General | Abdominal Pain (stomachache) | 11% | 2%
Digestive System | Loss of Appetite [Dose-related adverse reactions] | 36% | 2%
Nervous System | Insomnia | 12% | 4%
Metabolic/Nutritional | Weight Loss | 9% | 0%
Note: The following reactions did not meet the criterion for inclusion in Table 3 but were reported by 2% to 4% of adolescent patients receiving MAS ER with a higher incidence than patients receiving placebo in this study: accidental injury, asthenia (fatigue), dry mouth, dyspepsia, emotional lability, nausea, somnolence, and vomiting.

Table 4: Adverse Reactions Reported by 5% or More of Adults Receiving MAS ER with Higher Incidence Than Placebo in a 255 Patient Clinical Forced Weekly-Dose Titration Study [Included doses up to 60 mg.]
Body System | Preferred Term | MAS ER (n=191) | Placebo (n=64)
General | Headache | 26% | 13%
 | Asthenia | 6% | 5%
Digestive System | Dry Mouth | 35% | 5%
 | Loss of Appetite | 33% | 3%
 | Nausea | 8% | 3%
 | Diarrhea | 6% | 0%
Nervous System | Insomnia | 27% | 13%
 | Agitation | 8% | 5%
 | Anxiety | 8% | 5%
 | Dizziness | 7% | 0%
Cardiovascular System | Tachycardia | 6% | 3%
Metabolic/Nutritional | Weight Loss | 10% | 0%
Urogenital System | Urinary Tract Infection | 5% | 0%
Note: The following reactions did not meet the criterion for inclusion in Table 4 but were reported by 2% to 4% of adult patients receiving MAS ER with a higher incidence than patients receiving placebo in this study: infection, photosensitivity reaction, constipation, tooth disorder (e.g., teeth clenching, tooth infection), emotional lability, libido decreased, somnolence, speech disorder (e.g., stuttering, excessive speech), palpitation, twitching, dyspnea, sweating, dysmenorrhea, and impotence.

6.2 Adverse Reactions from Clinical Trials and Spontaneous Postmarketing Reports of Other Amphetamine Products

The following adverse reactions are from clinical trials and spontaneous postmarketing reports of other amphetamine products in pediatric patients and adults with ADHD. Because some of these reactions were reported voluntarily from a population of uncertain size, it is not always possible to estimate their frequency reliably or to establish a causal relationship to drug exposure.

Cardiovascular: Palpitations, sudden death, myocardial infarction. There have been isolated reports of cardiomyopathy associated with chronic amphetamine use.

Central Nervous System: Restlessness, irritability, euphoria, dyskinesia, dysphoria, depression, tremor, aggression, anger, logorrhea, paresthesia (including formication), motor and verbal tics.

Eye Disorders: Vision blurred, mydriasis.

Gastrointestinal: Unpleasant taste, constipation, intestinal ischemia, other gastrointestinal disturbances.

Allergic: Urticaria, rash, hypersensitivity reactions including angioedema and anaphylaxis. Serious skin rashes, including Stevens-Johnson Syndrome and toxic epidermal necrolysis have been reported.

Endocrine: Impotence, change in libido, frequent or prolonged erections.

Skin: Alopecia.

Musculoskeletal, Connective Tissue, and Bone Disorders: rhabdomyolysis.

Psychiatric Disorders: dermatillomania, bruxism.

Vascular Disorders: Raynaud's phenomenon.

7. DRUG INTERACTIONS

7.2 Drug/Laboratory Test Interactions

Amphetamines can cause a significant elevation in plasma corticosteroid levels. This increase is greatest in the evening. Amphetamines may interfere with urinary steroid determinations.

7.1 Drugs Having Clinically Important Interactions with Amphetamines

Table 5: Drugs having clinically important interactions with amphetamines.
MAO Inhibitors (MAOI)
Clinical Impact | MAOI antidepressants slow amphetamine metabolism, increasing amphetamines effect on the release of norepinephrine and other monoamines from adrenergic nerve endings causing headaches and other signs of hypertensive crisis. Toxic neurological effects and malignant hyperpyrexia can occur, sometimes with fatal results.
Intervention | Do not administer ADZENYS XR-ODT during or within 14 days following the administration of MAOI [see Contraindications (4)].
Serotonergic Drugs
Clinical Impact | The concomitant use of ADZENYS XR-ODT and serotonergic drugs increases the risk of serotonin syndrome.
Intervention | Initiate with lower doses and monitor patients for signs and symptoms of serotonin syndrome, particularly during ADZENYS XR-ODT initiation or dosage increase. If serotonin syndrome occurs, discontinue ADZENYS XR-ODT and the concomitant serotonergic drug(s) [see Warnings and Precautions (5.7)] .
Alkalinizing Agents
Clinical Impact | Increase blood levels and potentiate the action of amphetamine.
Intervention | Co-administration of ADZENYS XR-ODT and gastrointestinal alkalinizing agents should be avoided.
Acidifying Agents
Clinical Impact | Lower blood levels and efficacy of amphetamines.
Intervention | Increase dose based on clinical response.
Tricyclic Antidepressants
Clinical Impact | May enhance the activity of tricyclic or sympathomimetic agents causing striking and sustained increases in the concentration of d-amphetamine in the brain; cardiovascular effects can be potentiated.
Intervention | Monitor frequently and adjust or use alternative therapy based on clinical response.

8. USE IN SPECIFIC POPULATIONS

.

8.2 Lactation

Risk Summary

Based on limited case reports in published literature, amphetamine (d- or d, l-) is present in human milk at relative infant doses of 2% to 13.8% of the maternal weight-adjusted dosage and a milk/plasma ratio ranging between 1.9 and 7.5. There are no reports of adverse effects on the breastfed infant. Long-term neurodevelopmental effects on infants from amphetamine exposure are unknown. It is possible that large dosages of amphetamine might interfere with milk production, especially in women whose lactation is not well established. Because of the potential for serious adverse reactions in nursing infants, advise patients that breastfeeding is not recommended during treatment with ADZENYS XR-ODT.

8.1 Pregnancy

Pregnancy Exposure Registry

There is a pregnancy exposure registry that monitors outcomes in women exposed to ADHD medications, including ADZENYS XR-ODT, during pregnancy. Healthcare providers are encouraged to advise patients to register by contacting the National Pregnancy Registry for ADHD Medication at 1-866-961-2388 or online at www.womensmentalhealth.org/pregnancyregistry.

Risk Summary

Available data from epidemiologic studies and postmarketing reports on the use of amphetamine in pregnant women over decades of use have not identified a drug-associated risk of major birth defects or miscarriage. Neonates exposed to amphetamine in utero are at risk for withdrawal symptoms following delivery. Adverse pregnancy outcomes including premature delivery and low birth weight have been seen in infants born to mothers taking amphetamines during pregnancy (see Clinical Considerations).

No apparent effects on morphological development were observed in embryo-fetal development studies, with oral administration of amphetamine to rats and rabbits during organogenesis. However, in a pre- and post-natal development study, amphetamine (d- to l- ratio of 3:1) administered orally to pregnant rats during gestation and lactation caused a decrease in pup survival and a decrease in pup body weight that correlated with a delay in developmental landmarks at clinically relevant doses of amphetamine. In addition, adverse effects on reproductive performance were observed in pups whose mothers were treated with amphetamine. Long-term neurochemical and behavioral effects have also been reported in animal developmental studies using clinically relevant doses of amphetamine (see Data).

The background risk of major birth defects and miscarriage for the indicated population is unknown. All pregnancies have a background risk of birth defect, loss, or other adverse outcomes. In the U.S. general population, the estimated background risk of major birth defects and miscarriage in clinically recognized pregnancies is 2 to 4% and 15 to 20%, respectively.

Clinical Considerations

Fetal/Neonatal Adverse Reactions

Amphetamines, such as ADZENYS XR-ODT, cause vasoconstriction and thereby may decrease placental perfusion. In addition, amphetamines can stimulate uterine contractions, increasing the risk of premature delivery. Infants born to mothers taking amphetamines during pregnancy have an increased risk of premature delivery and low birth weight.

Monitor infants born to mothers taking amphetamines for symptoms of withdrawal such as feeding difficulties, irritability, agitation, and excessive drowsiness.

Data

Animal Data

Amphetamine, in the enantiomer ratio present in ADZENYS XR-ODT, (d- to l- ratio of 3:1), had no apparent effects on embryofetal morphological development or survival when orally administered to pregnant rats and rabbits throughout the period of organogenesis at doses of up to 6 and 16 mg/kg/day, respectively. These doses are approximately 2 and 12 times, respectively, the maximum recommended human dose (MRHD) for adolescents of 12.5 mg/day (as base), on a mg/m2 body surface area basis. Fetal malformations and death have been reported in mice following parenteral administration of d-amphetamine doses of 50 mg/kg/day (approximately 10 times the MRHD for adolescents on a mg/m2 basis) or greater to pregnant animals. Administration of these doses was also associated with severe maternal toxicity.

A study was conducted in which pregnant rats received daily oral doses of amphetamine (d- to l- enantiomer ratio of 3:1, the same as in ADZENYS XR-ODT) of 2, 6, and 10 mg/kg from gestation day 6 to lactation day 20. These doses are approximately 0.8, 2, and 4 times the MRHD for adolescents of 12.5 mg/day (as base), on a mg/m2 basis. All doses caused hyperactivity and decreased weight gain in the dams. A decrease in pup survival was seen at all doses. A decrease in pup bodyweight was seen at 6 and 10 mg/kg which correlated with delays in developmental landmarks. Increased pup locomotor activity was seen at 10 mg/kg on day 22 postpartum but not at 5 weeks post-weaning. When pups were tested for reproductive performance at maturation, gestational weight gain, number of implantations, and number of delivered pups were decreased in the group whose mothers had been given 10 mg/kg.

A number of studies in rodents indicate that prenatal or early postnatal exposure to amphetamine (d- or d, l-), at doses similar to those used clinically, can result in long-term neurochemical and behavioral alterations. Reported behavioral effects include learning and memory deficits, altered locomotor activity, and changes in sexual function.

8.5 Geriatric Use

ADZENYS XR-ODT has not been studied in the geriatric population.

8.4 Pediatric Use

The safety and effectiveness have been established in pediatric patients with ADHD ages 6 to 17 years of age in three adequate and well-controlled clinical trials of up to 4 weeks in duration [see Adverse Reactions (6.1), Clinical Pharmacology (12), Clinical Studies (14)].

The safety and efficacy of ADZENYS XR-ODT in pediatric patients less than 6 years have not been established.

In studies evaluating extended-release amphetamine products, patients 4 to <6 years of age had higher systemic amphetamine exposures than those observed in older pediatric patients at the same dosage. Pediatric patients 4 to <6 years of age also had a higher incidence of adverse reactions, including weight loss.

Long-Term Growth Suppression

Growth should be monitored during treatment with stimulants, including ADZENYS XR-ODT, in pediatric patients aged 6 to 17 years who are not growing or gaining weight as expected may need to have their treatment interrupted [see Warnings and Precautions (5.5)].

Juvenile Animal Data

In a juvenile developmental study, rats received daily oral doses of amphetamine (d to l enantiomer ratio of 3:1, the same as in ADZENYS XR-ODT) of 2, 6, or 20 mg/kg on days 7 to 13 of age; from day 14 to approximately day 60 of age these doses were given twice daily for total daily doses of 4, 12, or 40 mg/kg. The latter doses are approximately 0.6, 2, and 6 times the maximum recommended human dose for children of 18.8 mg/day (as base), on a mg/m^2 basis. Post dosing hyperactivity was seen at all doses; motor activity measured prior to the daily dose was decreased during the dosing period but the decreased motor activity was largely absent after an 18 day drug-free recovery period. Performance in the Morris water maze test for learning and memory was impaired at the 40 mg/kg dose, and sporadically at the lower doses, when measured prior to the daily dose during the treatment period; no recovery was seen after a 19 day drug-free period. A delay in the developmental milestones of vaginal opening and preputial separation was seen at 40 mg/kg but there was no effect on fertility.

9. DRUG ABUSE AND DEPENDENCE

9.1 Controlled Substance

ADZENYS XR-ODT contains amphetamine, a Schedule II controlled substance.

9.2 Abuse

ADZENYS XR-ODT has a high potential for abuse and misuse which can lead to the development of a substance use disorder, including addiction [see Warnings and Precautions (5.1)]. ADZENYS XR-ODT can be diverted for non-medical use into illicit channels or distribution.

Abuse is the intentional non-therapeutic use of a drug, even once, to achieve a desired psychological or physiological effect. Misuse is the intentional use, for therapeutic purposes, of a drug by an individual in a way other than prescribed by a health care provider or for whom it was not prescribed. Drug addiction is a cluster of behavioral, cognitive, and physiological phenomena that may include a strong desire to take the drug, difficulties in controlling drug use (e.g., continuing drug use despite harmful consequences, giving a higher priority to drug use than other activities and obligations), and possible tolerance or physical dependence.

Misuse and abuse of amphetamine may cause increased heart rate, respiratory rate, or blood pressure; sweating; dilated pupils; hyperactivity; restlessness; insomnia; decreased appetite; loss of coordination; tremors; flushed skin; vomiting; and/or abdominal pain. Anxiety, psychosis, hostility, aggression, and suicidal or homicidal ideation have also been observed with CNS stimulants abuse and/or misuse. Misuse and abuse of CNS stimulants, including ADZENYS XRODT, can result in overdose and death [see Overdosage (10)], and this risk is increased with higher doses or unapproved methods of administration, such as snorting or injection.

9.3 Dependence

Physical Dependence
ADZENYS XR-ODT may produce physical dependence. Physical dependence is a state that develops as a result of physiological adaptation in response to repeated drug use, manifested by withdrawal signs and symptoms after abrupt discontinuation or a significant dose reduction of a drug.

Withdrawal signs and symptoms after abrupt discontinuation or dose reduction following prolonged use of CNS stimulants including ADZENYS XR-ODT include dysphoric mood; depression; fatigue; vivid, unpleasant dreams; insomnia or hypersomnia; increased appetite; and psychomotor retardation or agitation.

Tolerance
ADZENYS XR-ODT may produce tolerance. Tolerance is a physiological state characterized by a reduced response to a drug after repeated administration (i.e., a higher dose of a drug is required to produce the same effect that was once obtained at a lower dose).

11. DESCRIPTION

ADZENYS XR-ODT (amphetamine extended-release orally disintegrating tablet) contains a 3 to 1 ratio of d- to l-amphetamine, a central nervous system stimulant.

The labeled strengths reflect the amount of amphetamine base in ADZENYS XR-ODT whereas the strengths of the (mixed salts of a single-entity amphetamine) products are in terms of the amount of amphetamine salts. Table 1 in Section 2.5 details the equivalent amounts of active ingredient in these products.

Structural Formula:

C9H13N MW 135.21

ADZENYS XR-ODT is an extended-release orally disintegrating tablet containing 50% immediate-release and 50% delayed-release amphetamine for once daily dosing.

ADZENYS XR-ODT also contains the following inactive ingredients: Mannitol, Crospovidone, Microcrystalline Cellulose, Methacrylic Acid, Sodium Polystyrene Sulfonate, Citric Acid, Fructose, Orange Flavor, Colloidal Silicon Dioxide, Triethyl Citrate, Sucralose, Lake Blend Orange, Magnesium Stearate, and Polyethylene Glycol 3350.

10. OVERDOSAGE

Clinical Effects of Overdose
Overdose of CNS stimulants is characterized by the following sympathomimetic effects:

• Cardiovascular effects including tachyarrhythmias, and hypertension or hypotension. Vasospasm, myocardial infarction, or aortic dissection may precipitate sudden cardiac death. Takotsubo cardiomyopathy may develop.

• CNS effects including psychomotor agitation, confusion, and hallucination. Serotonin syndrome, seizures, cerebral vascular accidents, and coma may occur.
• Life-threatening hyperthermia (temperatures greater than 104ºF) and rhabdomyolysis may develop.

Overdose Management
Consider the possibility of multiple drug ingestion. The pharmacokinetic profile of ADZENYS XR-ODT should be considered when treating patients with overdose. Damphetamine is not dialyzable. Consider contacting the Poison Help line (1-800-222-1222) or a medical toxicologist for additional overdose management recommendations.

12. CLINICAL PHARMACOLOGY

12.1 Mechanism of Action

Amphetamines are non-catecholamine sympathomimetic amines with CNS stimulant activity. The mode of therapeutic action in ADHD is not known. Amphetamines are thought to block the reuptake of norepinephrine and dopamine into the presynaptic neuron and increase the release of these monoamines into the extraneuronal space.

12.3 Pharmacokinetics

Absorption

Following a single, 18.8 mg oral dose of ADZENYS XR-ODT in 40 healthy adult subjects in a crossover study under fasting conditions, d-amphetamine mean (±SD) peak plasma concentrations of 44.9 (±8.9) ng/mL occurred at a median time of 5.0 hours after dosing, and l-amphetamine mean (±SD) peak plasma concentrations of 14.5 (+ 3.0 ng/mL occurred at a median time of 5.25 hours after dosing (Figure 1).

Figure 1: Mean Concentration of D-Amphetamine and L-Amphetamine vs Time for ADZENYS XR-ODT (18.8 mg) and Mixed Salts of a Single-Entity Amphetamine Product Extended-Release Capsules (MAS ER 30 mg) in the Fasted State

The single dose pharmacokinetics of d-amphetamine under fed conditions are summarized (Table 6) from studies in healthy adults following an oral dose of 18.8 mg ADZENYS XR-ODT.

Table 6: d-Amphetamine PK Parameters (mean + SD) after ADZENYS XR-ODT 18.8 mg
PK parameter | Adults Fasted | Adults Fed [A high-fat meal was consumed 30 minutes prior to drug administration]
Tmax (hr) [Data presented as median (range)] | 5.00 (3.00-12.00) | 7.00 (3.00-16.00)
T1/2 (hr) | 11.25±2.0 | 11.33±2.0
Cmax (ng/ml) | 44.9±8.9 | 36.3±6.9
AUCinf (hr*ng/mL) | 876.9±182.4 | 856.3±166.1

A single dose of ADZENYS XR-ODT 18.8 mg provided comparable plasma concentration profiles of both d-amphetamine and l-amphetamine to mixed salts of a single-entity amphetamine product extended-release capsules (MAS ER) 30 mg.

The mean elimination half-life for d-amphetamine is 11 hours in adults and 9-10 hours in pediatric patients aged 6 to 12 years. For l-amphetamine, the mean elimination half-life in adults is 14 hours and 10-11 hours in pediatric patients aged 6 to 12 years. Mean weight-normalized clearance values for d-amphetamine and l-amphetamine decreased slightly with an increase in age.

Food Effect

Food does not affect the extent of absorption of d-amphetamine and l-amphetamine but caused a 19% reduction in Cmax. Food also prolonged the median tmax by approximately 2.0 hours for d-amphetamine and by 2.5 hours for l-amphetamine after administration of ADZENYS XR-ODT. These changes are not considered clinically significant.

Alcohol Effect

In an in vitro alcohol-induced dose dumping study, a substantial increase in amphetamine release occurred in the presence of 40% alcohol but not with 5%, 10% and 20% alcohol.

Elimination

Metabolism and Excretion

Amphetamine is reported to be oxidized at the 4 position of the benzene ring to form 4-hydroxyamphetamine, or on the side chain α or β carbons to form alpha-hydroxy-amphetamine or norephedrine, respectively. Norephedrine and 4-hydroxy-amphetamine are both active and each is subsequently oxidized to form 4-hydroxy-norephedrine. Alpha-hydroxy-amphetamine undergoes deamination to form phenylacetone, which ultimately forms benzoic acid and its glucuronide and the glycine conjugate hippuric acid. Although the enzymes involved in amphetamine metabolism have not been clearly defined, CYP2D6 is known to be involved with formation of 4-hydroxy-amphetamine. Since CYP2D6 is genetically polymorphic, population variations in amphetamine metabolism are a possibility.

Amphetamine is known to inhibit monoamine oxidase, whereas the ability of amphetamine and its metabolites to inhibit various P450 isozymes and other enzymes has not been adequately elucidated. In vitro experiments with human microsomes indicate minor inhibition of CYP2D6 by amphetamine and minor inhibition of CYP1A2, 2D6, and 3A4 by one or more metabolites. However, due to the probability of auto-inhibition and the lack of information on the concentration of these metabolites relative to in vivo concentrations, no predications regarding the potential for amphetamine or its metabolites to inhibit the metabolism of other drugs by CYP isozymes in vivo can be made.

With normal urine pHs, approximately half of an administered dose of amphetamine is recoverable in urine as derivatives of alpha-hydroxy-amphetamine and approximately another 30-40% of the dose is recoverable in urine as amphetamine itself. Since amphetamine has a pKa of 9 .9, urinary recovery of amphetamine is highly dependent on pH and urine flow rates. Alkaline urine pHs result in less ionization and reduced renal elimination, and acidic pHs and high flow rates result in increased renal elimination with clearances greater than glomerular filtration rates, indicating the involvement of active secretion. Urinary recovery of amphetamine has been reported to range from 1% to 75%, depending on urinary pH, with the remaining fraction of the dose hepatically metabolized. Consequently, both hepatic and renal dysfunction have the potential to inhibit the elimination of amphetamine and result in prolonged exposures. In addition, drugs that effect urinary pH are known to alter the elimination of amphetamine, and any decrease in amphetamine's metabolism that might occur due to drug interactions or genetic polymorphisms is more likely to be clinically significant when renal elimination is decreased [see Drug Interactions (7)].

Specific Populations

Comparison of the pharmacokinetics of d- and l-amphetamine after oral administration of MAS ER in pediatric patients (6-12 years) and adolescent (13-17 years) ADHD patients and healthy adult volunteers indicates that body weight is the primary determinant of apparent differences in the pharmacokinetics of d-and l-amphetamine across the age range. Systemic exposure measured by area under the curve to infinity (AUC∞) and maximum plasma concentration (Cmax) decreased with increases in body weight, while oral volume of distribution (VZ/F), oral clearance (CL/F), and elimination half-life (t1/2) increased with increases in body weight.

Pediatric Patients

The pharmacokinetics of ADZENYS XR-ODT in pediatric patients has been established based on the pharmacokinetics of MAS ER in pediatric patients. On a mg/kg weight basis, pediatric patients eliminate amphetamine faster than adults. The elimination half-life (t1/2) is approximately 1 hour shorter for d-amphetamine and 2 hours shorter for l-amphetamine in pediatric patients than in adults. However, for a given dose of MAS ER, pediatric patients had higher systemic exposure to amphetamine (Cmax and AUC) than adults which was attributed to the higher dose administered to pediatric patients on a mg/kg body weight basis compared to adults. Upon dose normalization on a mg/kg basis, pediatric patients showed 30% less systemic exposure compared to adults.

Gender

Systemic exposure to amphetamine was 20-30% higher in women (N=20) than in men (N=20) due to the higher dose administered to women on a mg/kg body weight basis. When the exposure parameters (Cmax and AUC) were normalized by dose (mg/kg), these differences diminished. Age and gender had no direct effect on the pharmacokinetics of d- and l-amphetamine.

Race

Formal pharmacokinetic studies for race have not been conducted. However, amphetamine pharmacokinetics appeared to be comparable among Caucasians (N=33), Blacks (N=8) and Hispanics (N=10).

13. NONCLINICAL TOXICOLOGY

13.1 Carcinogenesis, Mutagenesis, Impairment of Fertility

Carcinogenesis

No evidence of carcinogenicity was found in studies in which d,l-amphetamine (enantiomer ratio of 1:1) was administered to mice and rats in the diet for 2 years at doses of up to 30 mg/kg/day in male mice, 19 mg/kg/day in female mice, and 5 mg/kg/day in male and female rats. These doses are approximately 2.4, 1.5, and 0.8 times, respectively, the maximum recommended human dose for children of 18.8 mg/day (as base), on a mg/m^2 body surface area basis.

Mutagenesis

Amphetamine, in the enantiomer ratio present in ADZENYS XR-ODT (d- to l- ratio of 3:1), was not clastogenic in the mouse bone marrow micronucleus test in vivo and was negative when tested in the E. coli component of the Ames test in vitro. d ,l-Amphetamine (1:1 enantiomer ratio) has been reported to produce a positive response in the mouse bone marrow micronucleus test, an equivocal response in the Ames test, and negative responses in the in vitro sister chromatid exchange and chromosomal aberration assays.

Amphetamine, in the enantiomer ratio present in ADZENYS XR-ODT (d- to l- ratio of 3:1), did not adversely affect fertility or early embryonic development in the rat at doses of up to 20 mg/kg/day [approximately 8 times the maximum recommended human dose for adolescents of 12.5 mg/day (as base), on a mg/m^2 body surface area basis].

13.2 Animal Toxicology and/or Pharmacology

Acute administration of high doses of amphetamine (d- or d, l-) has been shown to produce long-lasting neurotoxic effects, including irreversible nerve fiber damage, in rodents. The significance of these findings to humans is unknown.

14. CLINICAL STUDIES

The safety and efficacy of ADZENYS XR-ODT has been established based on adequate and well-controlled studies of mixed salts of a single-entity amphetamine product extended-release capsules in the treatment of ADHD. Below is a description of the results of the adequate and well-controlled studies of mixed salts of a single-entity amphetamine product extended-release capsules (MAS ER) in the treatment of ADHD.

Pediatric Patients

A double-blind, randomized, placebo-controlled, parallel-group study was conducted in pediatric patients 6 to 12 years of age (N=584) who met DSM-IV criteria for ADHD (either the combined type or the hyperactive-impulsive type). Patients were randomized to fixed-dose treatment groups receiving final doses of 10, 20 or 30 mg of mixed salts of a single-entity amphetamine product extended-release capsules or placebo once daily in the morning for three weeks.

The primary efficacy variable was the Attention Deficit Hyperactivity Disorder-Rating Scale IV (ADHD-RS-IV) total score for the primary cohort. The ADHD-RS-IV is an 18-item scale that measures the core symptoms of ADHD. Significant improvements on the ADHD-RS-IV, based upon teacher ratings of attention and hyperactivity, were observed for all doses compared to patients who received placebo, for all three weeks, including the first week of treatment, when all subjects were receiving a dose of 10 mg/day. Patients who received MAS ER showed improvements on the ADHD-RS-IV total score in both morning and afternoon assessments compared to patients on placebo.

In a classroom analogue study, patients (N=51) receiving fixed doses of 10 mg, 20 mg or 30 mg MAS ER demonstrated statistically significant improvements on teacher-rated Swanson, Kotkin, Agler, M-Flynn, and Pelham (SKAMP) scale Attention and Deportment variables and Permanent Product Measure of Performance (PERMP) scales compared to patients treated with placebo. SKAMP is a validated 13-item teacher-rated scale that assesses manifestations of ADHD in a classroom setting. PERMP is a skill-adjusted math test that measure attention in ADHD.

A double-blind, randomized, multi-center, parallel-group, placebo-controlled study was conducted in pediatric patients 13 to 17 years of age (N=327) who met DSM-IV criteria for ADHD. The primary cohort of patients (n=287, weighing ≤ 75kg) was randomized to fixed-dose treatment groups and received four weeks of treatment. Patients were randomized to receive final doses of 10 mg, 20 mg, 30 mg, and 40 mg MAS ER or placebo once daily in the morning. Patients randomized to doses greater than 10 mg were titrated to their final doses by 10 mg each week. Improvements in the primary cohort were statistically significantly greater in all four primary cohort active treatment groups (MAS ER 10 mg, 20 mg, 30 mg, and 40 mg) compared with the placebo group. There was not adequate evidence that doses greater than 20 mg/day conferred additional benefit.

Adult Patients

A double-blind, randomized, placebo-controlled, parallel-group study was conducted in adults (N=255) who met DSM-IV criteria for ADHD. Patients were randomized to fixed-dose treatment groups receiving final doses of 20, 40, or 60 mg of MAS ER or placebo once daily in the morning for four weeks. Improvements, measured with the Attention Deficit Hyperactivity Disorder-Rating Scale (ADHD-RS) were observed at endpoint for MAS ER 20, 40 and 60 mg, compared to patients who received placebo for all four weeks. However, there was not adequate evidence that doses greater than 20 mg/day conferred additional benefit.

16. HOW SUPPLIED/STORAGE AND HANDLING

Storage

Store at 20°C to 25º C (68°F to 77º F). Excursions permitted to 15-30º C (59-86º F) [see USP Controlled Room Temperature]

Store ADZENYS XR-ODT blister packages in the rigid, plastic travel case provided after removal from the carton. To obtain additional travel cases, patients and health care professionals can call Neos Therapeutics, Inc., at 1-888-236-6816.

How Supplied

ADZENYS XR-ODT 3.1 mg extended release orally disintegrating tablet: round, orange to light orange mottled (debossed A1 on one side), carton containing 5 blister cards of 6 tablets each, for a total of 30 tablets, NDC 70165-005-30

ADZENYS XR-ODT 6.3 mg extended release orally disintegrating tablet: round, orange to light orange mottled (debossed A2 on one side), carton containing 5 blister cards of 6 tablets each, for a total of 30 tablets, NDC 70165-010-30

ADZENYS XR-ODT 9.4 mg extended release orally disintegrating tablet: round, orange to light orange mottled (debossed A3 on one side), carton containing 5 blister cards of 6 tablets each, for a total of 30 tablets, NDC 70165-015-30

ADZENYS XR-ODT 12.5 mg extended release orally disintegrating tablet: round, orange to light orange mottled (debossed A4 on one side), carton containing 5 blister cards of 6 tablets each, for a total of 30 tablets, NDC 70165-020-30

ADZENYS XR-ODT 15.7 mg extended release orally disintegrating tablet: round, orange to light orange mottled (debossed A5 on one side), carton containing 5 blister cards of 6 tablets each, for a total of 30 tablets, NDC 70165-025-30

ADZENYS XR-ODT 18.8 mg extended release orally disintegrating tablet: round, orange to light orange mottled (debossed A6 on one side), carton containing 5 blister cards of 6 tablets each, for a total of 30 tablets, NDC 70165-030-30

MEDICATION GUIDE
ADZENYS XR-ODT (add-ZEN-iss)
amphetamine
extended-release orally disintegrating tablets, CII

What is the most important information I should know about ADZENYS XR-ODT?
ADZENYS XR-ODT may cause serious side effects, including:

- Abuse, misuse, and addiction. ADZENYS XR-ODT has a high chance for abuse and misuse and may lead to substance use problems, including addiction. Misuse and abuse of ADZENYS XR-ODT, other amphetamine containing medicines, and methylphenidate containing medicines, can lead to overdose and death. The risk of overdose and death is increased with higher doses of ADZENYS XR-ODT or when it is used in ways that are not approved, such as snorting or injection.
- Your healthcare provider should check you or your child’s risk for abuse, misuse, and addiction before starting treatment with ADZENYS XR-ODT and will monitor you or your child during treatment.
- ADZENYS XR-ODT may lead to physical dependence after prolonged use, even if taken as directed by your healthcare provider.
- Do not give ADZENYS XR-ODT to anyone else. See “ What is ADZENYS XR-ODT?” for more information.
- Keep ADZENYS XR-ODT in a safe place and properly dispose of any unused medicine. See “ How should I store ADZENYS XR-ODT?” for more information.
- Tell your healthcare provider if you or your child have ever abused or been dependent on alcohol, prescription medicines, or street drugs.
- Risks for people with serious heart disease. Sudden death has happened in people who have heart defects or other serious heart disease.

Your healthcare provider should check you or your child carefully for heart problems before starting ADZENYS XR-ODT. Tell your healthcare provider if you or your child has any heart problems, heart disease, or heart defects.

Call your healthcare provider or go to the nearest hospital emergency room right away if you or your child has any signs of heart problems such as chest pain, shortness of breath, or fainting while taking ADZENYS XR-ODT.

- Increased blood pressure and heart rate.

Your healthcare provider should check you or your child’s blood pressure and heart rate regularly during treatment with ADZENYS XR-ODT.

- Mental (Psychiatric) problems:

All Patients

- new or worse behavior and thought problems
- new or worse bipolar illness
- new psychotic symptoms (such as hearing voices, believing things that are not true, are suspicious) or new manic symptoms.

Tell your healthcare provider about any mental problems you or your child have, or about a family history of suicide, bipolar illness, or depression.

Call your healthcare provider right away if you or your child have any new or worsening mental symptoms or problems while taking ADZENYS XR-ODT, especially seeing or hearing things that are not real, believing things that are not real, or are suspicious.

What is ADZENYS XR-ODT?

ADZENYS XR-ODT is a central nervous system (CNS) stimulant prescription medicine. It is used for the treatment of Attention-Deficit Hyperactivity Disorder (ADHD). ADZENYS XR-ODT may help increase attention and decrease impulsiveness and hyperactivity in patients with ADHD.

ADZENYS XR-ODT is not recommended for use in children under 6 years of age with ADHD.

ADZENYS XR-ODTis a federally controlled substance (CII) because it contains amphetamine that can be a target for people who abuse prescription medicines or street drugs. Keep ADZENYS XR-ODT in a safe place to prevent it from theft. Never give your ADZENYS XR-ODT to anyone else, because it may harm them. Selling or giving away ADZENYS XR-ODT may harm others and is against the law.

Who should not take ADZENYS XR-ODT?
ADZENYS XR-ODT should not be taken if you or your child:

- are allergic to amphetamine, or any of the ingredients in ADZENYS XR-ODT. See the end of this Medication Guide for a complete list of ingredients in ADZENYS XR-ODT.
- are taking or have taken within the past 14 days an anti-depression medicine called monoamine oxidase inhibitor or MAOI.

What should I tell my healthcare provider before taking ADZENYS XR-ODT?
ADZENYS XR-ODT may not be right for you or your child. Before starting ADZENYS XR-ODT, tell your or your child’s healthcare provider about all health conditions (or a family history of) including:

- heart problems, heart disease, heart defects, or high blood pressure
- mental problems including psychosis, mania, bipolar illness, or depression
- circulation problems in fingers and toes

Tell your healthcare provider:

- if you or your child have kidney problems. Your healthcare provider may lower the dose.
- have or had repeated movements or sounds (tics) or Tourette’s syndrome, or have a family history of tics or Tourette’s syndrome.
- if you or your child are pregnant, or plan to become pregnant. It is not known if ADZENYS XR-ODT will harm your unborn baby. • There is a pregnancy registry for women who are exposed to ADZENYS XR-ODT during pregnancy. The purpose of the registry is to collect information about the health of females exposed to ADZENYS XR-ODT and their babies. If you or your child becomes pregnant during treatment with ADZENYS XR-ODT, talk to your healthcare provider about registering with the National Pregnancy Registry for Psychostimulants. You can register by calling 1-866-961-2388 or by visiting online at https://womensmentalhealth.org/clinical-and-research-programs/pregnancyregistry/othermedications/.
- if you or your child is breastfeeding or plan to breastfeed. ADZENYS XR-ODT passes into breast milk. You should not breastfeed while you are taking ADZENYS XR-ODT. Talk to your healthcare provider about the best way to feed the baby during treatment with ADZENYS XR-ODT.

Tell your healthcare provider about all of the medicines that you or your child takes including prescription and over-the-counter medicines, vitamins, and herbal supplements. ADZENYS XR-ODT and some medicines may interact with each other and cause serious side effects. Sometimes the doses of other medicines will need to be adjusted while taking ADZENYS XR-ODT.

Your healthcare provider will decide whether ADZENYS XR-ODT can be taken with other medicines.

Especially tell your healthcare provider if you or your child takes:

- anti-depression medicines including MAOIs

Know the medicines that you or your child take. Keep a list of your medicines with you to show your healthcare provider and pharmacist.

Do not start any new medicine while taking ADZENYS XR-ODT without talking to your healthcare provider first.

How should ADZENYS XR-ODT be taken?

- Take ADZENYS XR-ODT exactly as prescribed. Your healthcare provider may adjust the dose until it is right for you or your child.
- Take ADZENYS XR-ODT 1 time each day in the morning.
  - Leave the tablet in the blister pack until you are ready to take or give it.
  - Use dry hands to open the blister pack.
  - Tear along the perforation, bend the blister where indicated and peel back the blister's labeled backing to take out the tablet. Do not push the tablet through the foil.
  - Place the tablet on the tongue.
  - Take ADZENYS XR-ODT as soon as you open the blister pack. The tablet will dissolve in your mouth (saliva) so that it can be swallowed.
  - Do not crush or chew.
- ADZENYS XR-ODT can be taken with or without food.

Your healthcare provider may do regular checks of your or your child’s blood, heart, and blood pressure while taking ADZENYS XR-ODT.

- Children should have their height and weight checked often while taking ADZENYS XR-ODT. ADZENYS XR-ODT treatment may be stopped if a problem is found during these check-ups.

If you or your child take too much ADZENYS XR-ODT, call your healthcare provider or Poison Help line at 1-800-222-1222 or go to the nearest hospital emergency room right away.

What should I avoid while taking ADZENYS XR-ODT?

- drinking alcohol

What are possible side effects of ADZENYS XR-ODT?

ADZENYS XR-ODT can cause serious side effects, including:

- See " What is the most important information I should know about ADZENYS XR-ODT?" for information on reported heart and mental problems.
- slowing of growth (height and weight) in children. Children should have their height and weight checked often during treatment with ADZENYS XR-ODT. Your healthcare provider may stop your child’s ADZENYS XR-ODT treatment if they are not growing or gaining weight as expected.
- Circulation problems in fingers and toes [Peripheral vasculopathy, including Raynaud's phenomenon]:
- fingers or toes may feel numb, cool, painful
- fingers or toes may change from pale, to blue, to red

Tell your healthcare provider if you have or your child has numbness, pain, skin color change, or sensitivity to temperature in your fingers or toes.

Call your healthcare provider right away if you have or your child has any unexplained wounds appearing on fingers or toes while taking ADZENYS XR-ODT.

- New or worsening tics or worsening Tourette’s syndrome. Tell your healthcare provider if you or your child get any new or worsening tics or worsening Tourette’s syndrome during treatment with ADZENYS XR-ODT.

Common side effects of ADZENYS XR-ODT include decreased appetite and problems sleeping .

Common side effects of ADZENYS XR-ODT in children 6 to 12 years of age also include:

- stomach pain
- nervousness

- extreme mood change
- nausea

- vomiting
- fever

Common side effects of ADZENYS XR-ODT in children 13 to 17 years of age also include:

- stomach pain

- weight loss

Common side effects of ADZENYS XR-ODT in adults also include:

- dry mouth
- nausea
- dizziness
- weakness

- headache
- anxiety
- fast heart beat
- urinary tract infections

- weight loss
- restlessness
- diarrhea

Talk to your doctor if you or your child have side effects that are bothersome or do not go away.

These are not all the possible side effects ADZENYS XR-ODT. Ask your doctor or pharmacist for more information.

Call your doctor for medical advice about side effects. You may report side effects to FDA at 1800-FDA-1088.

How should I store ADZENYS XR-ODT?

- Store ADZENYS XR-ODT at room temperature between 68° F to 77° F (20° C to 25° C).
- Store ADZENYS XR-ODT in a safe place, like a locked cabinet.
- Store ADZENYS XR-ODT in the blister packaging until you are ready to take or give it.
- Store ADZENYS XR-ODT blister packages in the hard plastic travel case provided after removal from the carton.
- Dispose of remaining, unused, or expired ADZENYS XR-ODT by a medicine take-back program at a U.S. Drug Enforcement Administration (DEA) authorized collection site. If no take-back program or DEA authorized collector is available, mix ADZENYS XR-ODT with an undesirable, nontoxic substance such as dirt, cat litter, or used coffee grounds to make it less appealing to children and pets. Place the mixture in a container such as a sealed plastic bag and throw away ADZENYS XR-ODT in the household trash. Visit www.fda.gov/drugdisposal for additional information on disposal of unused medicines.

Keep ADZENYS XR-ODT and all medicines out of the reach of children.

General information about the safe and effective use of ADZENYS XR-ODT
Medicines are sometimes prescribed for purposes other than those listed in the Medication Guide. Do not use ADZENYS XR-ODT for a condition for which it has not been prescribed. Do not give ADZENYS XR-ODT to other people, even if they have the same condition. It may harm them and it is against the law. This Medication Guide summarizes the most important information about ADZENYS XR-ODT. If you would like more information, talk with your healthcare provider. You can ask your pharmacist or healthcare provider for information about ADZENYS XR-ODT that is written for healthcare professionals.

For more information about ADZENYS XR-ODT or to get a plastic travel case contact Neos Therapeutics, Inc. at 1-888-236-6816 or go to www.adzenysxrodt.com.

What are the ingredients in ADZENYS XR-ODT?

Active Ingredients: Amphetamine

Inactive Ingredients: Mannitol, Crospovidone, Microcrystalline Cellulose, Methacrylic Acid, Sodium Polystyrene Sulfonate, Citric Acid, Fructose, Orange Flavor, Colloidal Silicon Dioxide, Triethyl Citrate, Sucralose,Lake Blend Orange, Magnesium Stearate, and Polyethylene Glycol 3350.

Manufactured for Neos Therapeutics Brands LLC, Denver, CO 80237. ADZENYS XR-ODT is registered in the US Patent and Trademark Office© 2016 Neos Therapeutics, Inc.

This Medication Guide has been approved by the U.S. Food and Drug Administration.

09/2025

17. PATIENT COUNSELING INFORMATION

Advise the patient to read the FDA-approved patient labeling (Medication Guide).

Dosage and Administration Instructions

Provide the following instructions on administration to the patient:

- The tablet should remain in the blister pack until the patient is ready to take it.
- The patient or caregiver should use dry hands to open the blister.
- Tear along the perforation, bend the blister where indicated and peel back the blister's labeled backing to take out the tablet. The tablet should not be pushed through the foil.
- As soon as the blister is opened, the tablet should be removed and placed on the patient's tongue.
- The whole tablet should be placed on the tongue and allowed to disintegrate without chewing or crushing.
- The tablet will disintegrate in saliva so that it can be swallowed.

Abuse, Misuse, and Addiction

Educate patients and their families about the risks of abuse, misuse, and addiction of ADZENYS XR-ODT, which can lead to overdose and death, and proper disposal of any unused drug [see Warnings and Precautions (5.1), Drug Abuse and Dependence (9.2), Overdosage (10)]. Advise patients to store ADZENYS XR-ODT in a safe place, preferably locked, and instruct patients to not give ADZENYS XR-ODT to anyone else.

Risks to Patients with Serious Cardiac Disease

Advise patients that there are potential risks to patients with serious cardiac disease, including sudden death, with ADZENYS XR-ODT use. Instruct patients to contact a healthcare provider immediately if they develop symptoms such as exertional chest pain, unexplained syncope, or other symptoms suggestive of cardiac disease [see Warnings and Precautions (5.2)].

Increased Blood Pressure and Heart Rate

Instruct patients that ADZENYS XR-ODT can cause elevations of their blood pressure and pulse rate [see Warnings and Precautions (5.3)].

Psychiatric Adverse Reactions

Advise patients that ADZENYS XR-ODT, at recommended doses, may cause psychotic symptoms or mania [see Warnings and Precautions (5.4)].

Long-Term Suppression of Growth

Advise patients that ADZENYS XR-ODT may cause slowing of growth and weight loss [see Warnings and Precautions (5.5)].

Circulation problems in Fingers and Toes [Peripheral vasculopathy, including Raynaud's phenomenon]

Instruct patients beginning treatment with ADZENYS XR-ODT about the risk of peripheral vasculopathy, including Raynaud's phenomenon, and associated signs and symptoms: fingers or toes may feel numb, cool, painful, and/or may change color from pale, to blue, to red.

Instruct patients to report to their physician any new numbness, pain, skin color change, or sensitivity to temperature in fingers or toes.

Instruct patients to call their physician immediately with any signs of unexplained wounds appearing on fingers or toes while taking ADZENYS XR-ODT.

Further clinical evaluation (e.g., rheumatology referral) may be appropriate for certain patients [see Warnings and Precautions (5.6)].

Serotonin Syndrome

Caution patients about the risk of serotonin syndrome with concomitant use of ADZENYS XR-ODT and other serotonergic drugs including SSRIs, SNRIs, triptans, tricyclic antidepressants, fentanyl, lithium, tramadol, tryptophan, buspirone, St. John's Wort, and with drugs that impair metabolism of serotonin (in particular MAOIs, both those intended to treat psychiatric disorders and also others such as linezolid [see Contraindications (4), Warnings and Precautions (5.7) and Drug Interactions (7.1)] . Advise patients to contact their healthcare provider or report to the emergency room if they experience signs or symptoms of serotonin syndrome.

Concomitant Medications

Advise patients to notify their physicians if they are taking, or plan to take, any prescription or over-the-counter drugs because there is a potential for interactions [see Drug Interactions (7.1)] .

Pregnancy

Advise patients that there is a pregnancy exposure registry that monitors pregnancy outcomes in women exposed to ADZENYS XR-ODT during pregnancy. Advise patients to notify their healthcare provider if they become pregnant or intend to become pregnant during treatment with ADZENYS XR-ODT. Advise patients of the potential fetal effects from the use of ADZENYS XR-ODT during pregnancy. [see Use in Specific Populations (8.1) ] .

Lactation

Advise patients not to breastfeed if they are taking ADZENYS XR-ODT [see Use in Specific Populations (8.2)].

Alcohol

Advise patients to avoid alcohol while taking ADZENYS XR-ODT. Consumption of alcohol while taking ADZENYS XR-ODT may result in a more rapid release of the dose of amphetamine [see Clinical Pharmacology (12) ] .

Manufactured for Neos Therapeutics Brands, LLC., Denver, CO 80237. Made in USA.

For more information call 1-888-319-1789.

ADZENYS XR-ODT is a registered trademark of Neos Therapeutics, Inc.

Copyright© 2017, Neos Therapeutics, Inc.

Patent Number 8,709,491 B2

Motor and Verbal Tics, and Worsening of Tourette’s Syndrome
Advise patients that motor and verbal tics and worsening of Tourette’s syndrome may occur during treatment with ADZENYS XR-ODT. Instruct patients to notify their healthcare provider if emergence of new tics or worsening of tics or Tourette’s syndrome occurs [see Warnings and Precautions (5.8)].

PRINCIPAL DISPLAY PANEL - 3.1 mg Tablet Blister Pack Carton

NDC 70165-005-30

Contains:
30 Tablets (5 x 6-count blister cards)
Travel Case

Rx Only

Adzenys XR-ODT™ CII
Amphetamine Extended-Release
Orally Disintegrating Tablets

Do not crush or chew tablets

Each tablet contains 3.1 mg of amphetamine
(equivalent to that in a 5 mg strength mixed salts
of a single-entity amphetamine product)

3.1 mg

NEOS™
Therapeutics

PHARMACIST: Dispense the enclosed Medication Guide to each patient.

PRINCIPAL DISPLAY PANEL - 6.3 mg Tablet Blister Pack Carton

NDC 70165-010-30

Contains:
30 Tablets (5 x 6-count blister cards)
Travel Case

Rx Only

Adzenys XR-ODT™ CII
Amphetamine Extended-Release
Orally Disintegrating Tablets

Do not crush or chew tablets

Each tablet contains 6.3 mg of amphetamine
(equivalent to that in a 10 mg strength mixed salts
of a single-entity amphetamine product)

6.3 mg

NEOS™
Therapeutics

PHARMACIST: Dispense the enclosed Medication Guide to each patient.

PRINCIPAL DISPLAY PANEL - 9.4 mg Tablet Blister Pack Carton

NDC 70165-015-30

Contains:
30 Tablets (5 x 6-count blister cards)
Travel Case

Rx Only

Adzenys XR-ODT™ CII
Amphetamine Extended-Release
Orally Disintegrating Tablets

Do not crush or chew tablets

Each tablet contains 9.4 mg of amphetamine
(equivalent to that in a 15 mg strength mixed salts
of a single-entity amphetamine product)

9.4 mg

NEOS™
Therapeutics

PHARMACIST: Dispense the enclosed Medication Guide to each patient.

PRINCIPAL DISPLAY PANEL - 12.5 mg Tablet Blister Pack Carton

NDC 70165-020-30

Contains:
30 Tablets (5 x 6-count blister cards)
Travel Case

Rx Only

Adzenys XR-ODT™ CII
Amphetamine Extended-Release
Orally Disintegrating Tablets

Do not crush or chew tablets

Each tablet contains 12.5 mg of amphetamine
(equivalent to that in a 20 mg strength mixed salts
of a single-entity amphetamine product)

12.5 mg

NEOS™
Therapeutics

PHARMACIST: Dispense the enclosed Medication Guide to each patient.

PRINCIPAL DISPLAY PANEL - 15.7 mg Tablet Blister Pack Carton

NDC 70165-025-30

Contains:
30 Tablets (5 x 6-count blister cards)
Travel Case

Rx Only

Adzenys XR-ODT™ CII
Amphetamine Extended-Release
Orally Disintegrating Tablets

Do not crush or chew tablets

Each tablet contains 15.7 mg of amphetamine
(equivalent to that in a 25 mg strength mixed salts
of a single-entity amphetamine product)

15.7 mg

NEOS™
Therapeutics

PHARMACIST: Dispense the enclosed Medication Guide to each patient.

PRINCIPAL DISPLAY PANEL - 18.8 mg Tablet Blister Pack Carton

NDC 70165-030-30

Contains:
30 Tablets (5 x 6-count blister cards)
Travel Case

Rx Only

Adzenys XR-ODT™ CII
Amphetamine Extended-Release
Orally Disintegrating Tablets

Do not crush or chew tablets

Each tablet contains 18.8 mg of amphetamine
(equivalent to that in a 30 mg strength mixed salts
of a single-entity amphetamine product)

18.8 mg

NEOS™
Therapeutics

PHARMACIST: Dispense the enclosed Medication Guide to each patient.